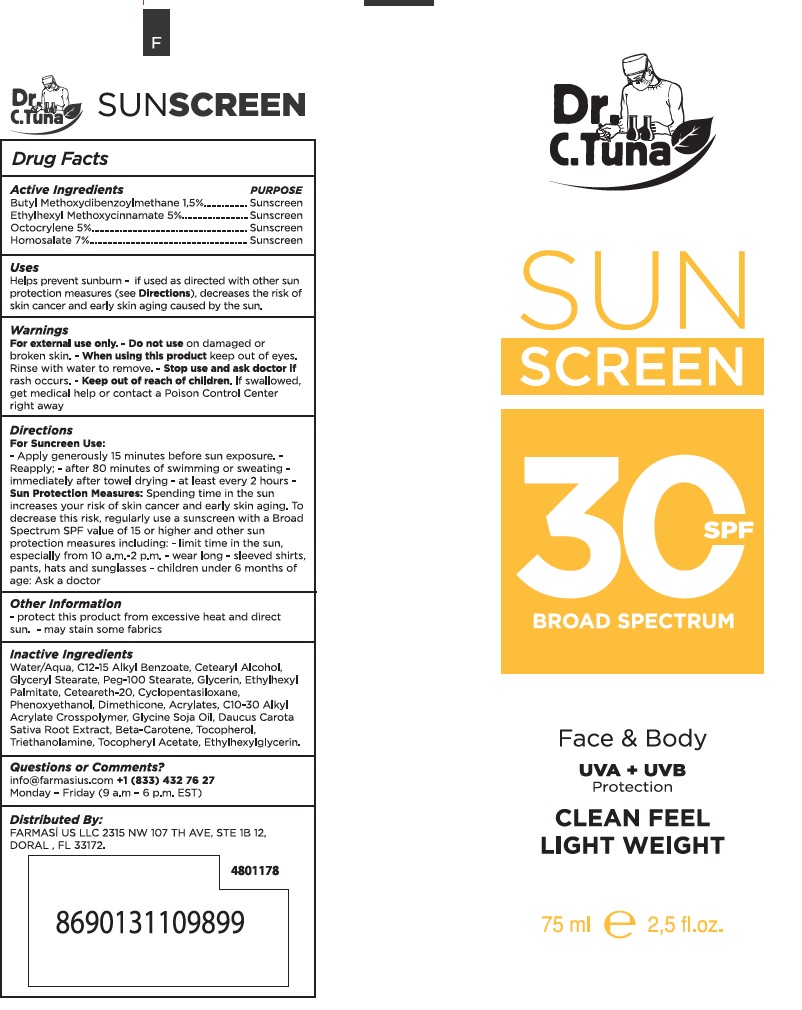 DRUG LABEL: Dr. C. Tuna Sunscreen SPF30 Broad Spectrum
NDC: 74690-001 | Form: LOTION
Manufacturer: Farmasi US LLC
Category: otc | Type: HUMAN OTC DRUG LABEL
Date: 20260109

ACTIVE INGREDIENTS: OCTINOXATE 50 mg/1 mL; OCTOCRYLENE 50 mg/1 mL; HOMOSALATE 70 mg/1 mL; AVOBENZONE 15 mg/1 mL
INACTIVE INGREDIENTS: WATER; ALKYL (C12-15) BENZOATE; CETOSTEARYL ALCOHOL; GLYCERYL MONOSTEARATE; PEG-100 STEARATE; GLYCERIN; ETHYLHEXYL PALMITATE; POLYOXYL 20 CETOSTEARYL ETHER; CYCLOMETHICONE 5; PHENOXYETHANOL; DIMETHICONE; CARBOMER INTERPOLYMER TYPE A (ALLYL SUCROSE CROSSLINKED); ACRYLIC ACID; SOYBEAN OIL; CARROT; BETA CAROTENE; TOCOPHEROL; TROLAMINE; .ALPHA.-TOCOPHEROL ACETATE; ETHYLHEXYLGLYCERIN

Dr. C. Tuna Sunscreen SPF30 Broad Spectrum

Active Ingredients

Butyl Methoxydibenzoylmethane 1.5%

Ethylhexyl Methoxycinnamate 5%

Octocrylene 5%

Homosalate 7%

Purpose

Sunscreen

Uses

Helps prevent sunburn - if used as directed with other sun protection measures (see), decreases the risk of skin cancer and early skin aging casued by the sun. Directions

Warnings

For external use only.

-Do not use

on damaged or broken skin.

-When using this product

keep out of eyes. Rinse with water to remove.

- Stop use and ask doctor if

rash occurs.

- Keep out of reach of children.

If swallowed, get medical help or contact a Poison Control Center right away

Directions

For Suncreen Use:

-Apply generously 15 minutes before sun exposure.-Reapply; - after 80 minutes of swimming or sweating - immediately after towel drying - at least every 2 hours

Spending time in the sun increases your risk of skin cancer and early skin aging. To decrease this risk, regullarly use a sunscreen with a Broad Spectrum SPF value of 15 or higher and other sun protection measures including: - limit time in the sun, especially from 10 a.m- 2 p.m. - wear long - sleeved shirts, pants, hats and sunglasses - children under 6 months of age: Ask a doctor - Sun Protection Measures:

Other Information

- protect this product from excessive heat and direct sun. - may stain some fabrics

Inactive Ingredients

Water/Aqua, C12-15 Alkyl Benzoate, Cetearyl Alcohol, Glyceryl Stearate, Peg-100 Stearate, Glycerin, Ethylhexyl Palmitate, Ceteareth-20, Cyclopentasiloxane, Phenoxyethanol, Dimethicone, Acrylates, C10-30 Alkyl Acrylate Crosspolymer, Glycine Soja Oil, Daucus Carota Sativa Root Extract, Beta-Carotene, Tocopherol, Triethanolamine, Tocopheryl Acetate, Ethylhexylglycerin.

Questions or Comments?

info@farmasius.com +1 (833) 432 76 27

Monday - Friday (9 a.m - 6p.m. EST)